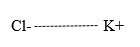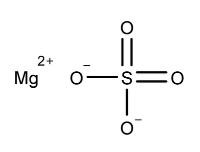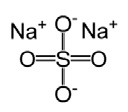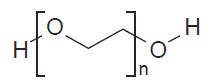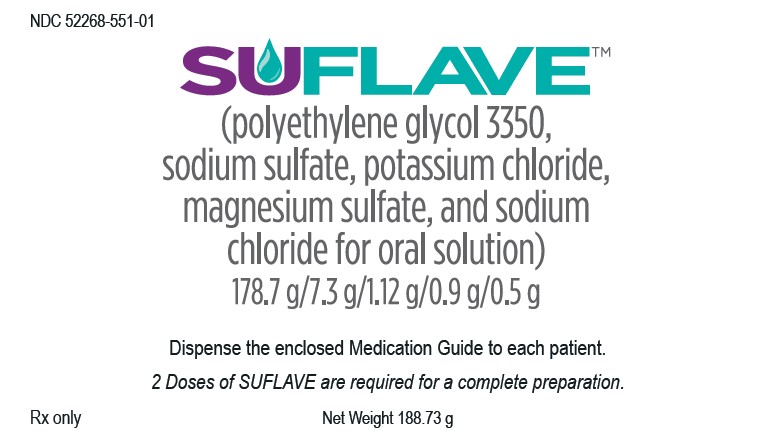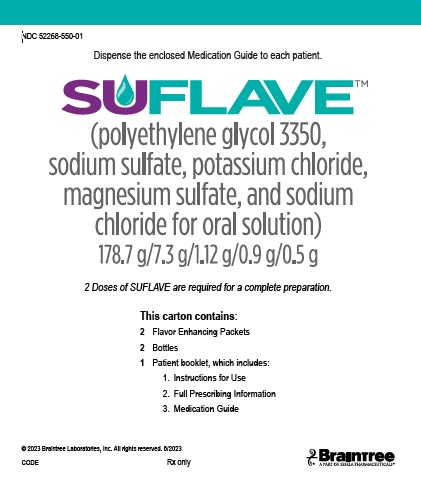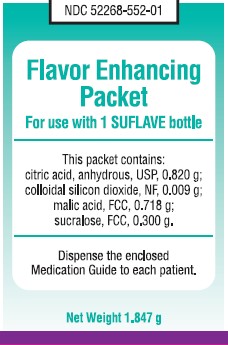 DRUG LABEL: SUFLAVE
NDC: 52268-550 | Form: KIT | Route: ORAL
Manufacturer: Braintree Laboratories, Inc.
Category: prescription | Type: HUMAN PRESCRIPTION DRUG LABEL
Date: 20230615

ACTIVE INGREDIENTS: POLYETHYLENE GLYCOL 3350 178.7 g/1 1; SODIUM SULFATE 7.3 g/1 1; POTASSIUM CHLORIDE 1.12 g/1 1; MAGNESIUM SULFATE ANHYDROUS 0.9 g/1 1; SODIUM CHLORIDE 0.5 g/1 1
INACTIVE INGREDIENTS: ADVANTAME; NEOTAME; MALIC ACID 0.718 g/1 1; ANHYDROUS CITRIC ACID 0.82 g/1 1; SUCRALOSE 0.3 g/1 1; SILICON DIOXIDE 0.009 g/1 1

HIGHLIGHTS OF PRESCRIBING INFORMATION

These highlights do not include all the information needed to use SUFLAVE®safely and effectively. See full prescribing information for SUFLAVE.
SUFLAVE (polyethylene glycol 3350, sodium sulfate, potassium chloride, magnesium sulfate, and sodium chloride for oral solution)
Initial U.S. Approval: 2023

1 INDICATIONS AND USAGE

SUFLAVE is an osmotic laxative indicated for cleansing of the colon in preparation for colonoscopy in adults.

2 DOSAGE AND ADMINISTRATION

Preparation and Administration (2.1)

- Administration of two doses of SUFLAVE are required for a complete preparation for colonoscopy.
- One dose of SUFLAVE is equal to one bottle plus one flavor enhancing packet.
- Each bottle must be reconstituted with water before ingestion.
- An additional 16 ounces of water must be consumed after each dose.
- Stop consumption of all fluids at least 2 hours before the colonoscopy.

Recommended Dosage and Administration (2.2)

- The recommended Split-Dose (two-day) regimen consists of two doses of SUFLAVE :
  o Day 1, Dose 1: Evening before Colonoscopy: 1 bottle with flavor enhancing packet
  o Day 2, Dose 2: Morning of the Colonoscopy (5 to 8 hours prior to the colonoscopy and no sooner than 4 hours from starting Dose 1):1 bottle with flavor enhancing packet
- For complete information on preparation before colonoscopy and administration of the dosage regimen, see full prescribing information. (2.1, 2.2)

3 DOSAGE FORMS AND STRENGTHS

For Oral Solution: Two bottles and two flavor enhancing packets.

- Each bottle contains 178.7 g polyethylene glycol 3350, 7.3 g sodium sulfate, 1.12 g potassium chloride, 0.9 g magnesium sulfate, and 0.5 g sodium chloride. The bottle also contains lemon-lime flavoring. (3)

4 CONTRAINDICATIONS

- Gastrointestinal obstruction or ileus (4, 5.6)
- Bowel perforation (4, 5.6)
- Toxic colitis or toxic megacolon (4)
- Gastric retention (4)
- Hypersensitivity to any ingredient in SUFLAVE (4)

5 WARNINGS AND PRECAUTIONS

- Risk of fluid and electrolyte abnormalities: Encourage adequate hydration, assess concurrent medications and consider laboratory assessments prior to and after each use. (5.1, 7.1)
- Cardiac arrhythmias: Consider pre-dose and post-colonoscopy ECGs in patients at increased risk. (5.2)
- Seizures: Use caution in patients with a history of seizures and patients at increased risk of seizures, including medications that lower the seizure threshold. (5.3, 7.1)
- Colonic mucosal ulcerations: Consider potential for ulcerations when interpreting colonoscopy findings in patients with known or suspected inflammatory bowel disease. (5.5)
- Patients with renal impairment or taking concomitant medications that affect renal function: Use caution, ensure adequate hydration and consider laboratory testing. (5.4, 7.1)
- Suspected GI obstruction or perforation: Rule out the diagnosis before administration. (4, 5.6)
- Patients at risk for aspiration: Observe during administration (5.7)
- Hypersensitivity reactions, including anaphylaxis: Inform patients to seek immediate medical care if symptoms occur (5.8)

6 ADVERSE REACTIONS

Most common adverse reactions (≥2%) are: nausea, abdominal distension, vomiting, abdominal pain and headache. (6.1)
To report SUSPECTED ADVERSE REACTIONS, contact Braintree Laboratories, Inc. at 1-800-874-6756 or FDA at 1-800-FDA-1088 or www.fda.gov/medwatch.

7 DRUG INTERACTIONS

Drugs that increase risk of fluid and electrolyte imbalance. (7.1)

FULL PRESCRIBING INFORMATION

1 INDICATIONS AND USAGE

SUFLAVE is indicated for the cleansing of the colon as a preparation for colonoscopy in adults.

2 DOSAGE AND ADMINISTRATION

2.1 Important Preparation and Administration Instructions

- Correct fluid and electrolyte abnormalities before treatment with SUFLAVE [see Warnings and Precautions (5.1)]
- Two doses of SUFLAVE are required for a complete preparation for colonoscopy. One dose of SUFLAVE is equal to one bottle plus one flavor enhancing packet.
- Reconstitue each bottle with water before ingestion. Do not reconstitute SUFLAVE with liquids other than water and/or add starch-based thickeners to the mixing bottle [see Warnings and Precautions (5.7)] .
- Must consume an additional 16 ounces of water after each dose of SUFLAVE.
- Consume a low residue breakfast on the day before colonoscopy. After breakfast, only consume clear liquids up to 2 hours prior to colonoscopy.
- Do not eat solid food or drink milk or eat or drink anything colored red or purple.
- Do not drink alcohol.
- Do not take other laxatives while taking SUFLAVE. [see Drug Interactions (7.3)].
- Do not take oral medications within 1 hour of starting each dose of SUFLAVE. [see Drug Interactions (7.2)].
- If taking tetracycline or fluoroquinolone antibiotics, iron, digoxin, chlorpromazine, or penicillamine, take these medications at least 2 hours before and not less than 6 hours after administration of each dose of SUFLAVE [see Drug Interactions (7.2)] .
- Stop consumption of all fluids at least 2 hours prior to the colonoscopy.
- If nausea, bloating, or abdominal cramping occurs, pause or slow the rate of drinking the solution and additional water until symptoms diminish.

2.2 Split-Dose (2-Day) Recommended Doasge

The recommended Split-Dose (two-day) regimen consists of two doses of SUFLAVE:

- Day 1, Dose 1: Evening before Colonoscopy: 1 bottle with flavor enhancing packet
- Day 2, Dose 2: Morning of the Colonoscopy (5 to 8 hours prior to the colonoscopy and no sooner than 4 hours from starting Dose 1): 1 bottle with flavor enhancing packet

2.3 Preparation and Administration Instructions

The Day Prior to Colonoscopy:

- A low residue breakfast may be consumed. Examples of low residue foods are white bread, biscuits, muffins (no wheat), cornflakes, eggs, cream of wheat, grits, yogurt, cottage cheese, coffee, tea, juice without pulp, fruit (no skin or seeds).
- After breakfast, only consume clear liquids until after the colonoscopy. Examples of clear liquids are water, fruit juice (without pulp), lemonade, plain coffee, tea (no cream or non-dairy creamer), chicken broth, gelatin dessert (no fruit or topping).
- No red or purple liquids, no milk or alcoholic beverages.

Day 1, Dose 1 - Early in the Evening Prior to Colonoscopy:

- Open 1 flavor enhancing packet and pour the contents into 1 bottle.
- Fill the provided bottle with lukewarm water up to the fill line. After capping the bottle, gently shake the bottle until all powder has dissolved. For best taste, refrigerate the solution for an hour before drinking. Do not freeze. Use within 24 hours.
- Drink 8 ounces of solution every 15 minutes until the bottle is empty.
- Drink an additional 16 ounces of water during the evening.

If nausea, bloating, or abdominal cramping occurs, pause or slow the rate of drinking the solution and additional water until symptoms diminish.

Day 2, Dose 2 - The Morning of the Colonoscopy (5 to 8 hours prior to the colonoscopy and no sooner than 4 hours from starting Dose 1):

Continue to consume only clear liquids until after the colonoscopy.

1. Repeat Step 1 to Step 3 from Day 1, Dose 1.
2. Drink an additional 16 ounces of water during the morning.

- Stop drinking liquids at least 2 hours prior to colonoscopy.
- If nausea, bloating, or abdominal cramping occurs, pause or slow the rate of drinking the solution and additional water until symptoms diminish.

Storage of Reconstituted Solution
After reconstitution, keep solution refrigerated 2°C to 8°C (36°F to 46°F). Do not freeze. Use within 24 hours, discard unused solution.

3 DOSAGE FORMS AND STRENGTHS

SUFLAVE is supplied as a white powder for reconstitution and is available in a carton that contains two bottles and two flavor enhancing packets.

- Each bottle contains 178.7 g polyethylene glycol 3350, 7.3 g sodium sulfate, 1.12 g potassium chloride, 0.9 g magnesium sulfate, and 0.5 g sodium chloride. The bottle contains lemon-lime flavoring.

When diluted as directed, the solution is slightly hazy to hazy.

4 CONTRAINDICATIONS

SUFLAVE is contraindicated in the following conditions:

- Gastrointestinal obstruction or ileus [see Warnings and Precautions (5.6)]
- Bowel perforation [see Warnings and Precautions (5.6)]
- Toxic colitis or toxic megacolon
- Gastric retention
- Hypersensitivity to any ingredient in SUFLAVE [see Warnings and Precautions (5.8)]

5 WARNINGS AND PRECAUTIONS

5.1 Serious Fluid and Electrolyte Abnormalities

Advise all patients to hydrate adequately before, during, and after the use of SUFLAVE. If a patient develops significant vomiting or signs of dehydration after taking SUFLAVE, consider performing post-colonoscopy lab tests (electrolytes, creatinine, and BUN).

Bowel preparation products can cause fluid and electrolyte disturbances, which can lead to serious adverse reactions including cardiac arrhythmias, seizures, and renal impairment [see Adverse Reactions (6.2)] . Correct fluid and electrolyte abnormalities before treatment with SUFLAVE. Use SUFLAVE with caution in patients with conditions, or who are using medications [such as diuretics, angiotensin converting enzyme (ACE) inhibitors or angiotensin receptor blockers (ARBs)], that increase the risk for fluid and electrolyte disturbances or may increase the risk of seizure, arrhythmias, and renal impairment [see Drug Interactions (7.1)] .

5.2 Cardiac Arrythmias

There have been rare reports of serious arrhythmias associated with the use of ionic osmotic laxative products for bowel preparation. These occur predominantly in patients with underlying cardiac risk factors and electrolyte disturbances. Use caution when prescribing SUFLAVE for patients at increased risk of arrhythmias (e.g., patients with a history of prolonged QT interval, uncontrolled arrhythmias, recent myocardial infarction, unstable angina, congestive heart failure, or cardiomyopathy). Consider pre-dose and post-colonoscopy ECGs in patients at increased risk of serious cardiac arrhythmias.

5.3 Seizures

There have been reports of generalized tonic-clonic seizures and/or loss of consciousness associated with use of bowel preparation products in patients with no prior history of seizures. The seizure cases were associated with electrolyte abnormalities (e.g., hyponatremia, hypokalemia, hypocalcemia, and hypomagnesemia) and low serum osmolality. The neurologic abnormalities resolved with correction of fluid and electrolyte abnormalities.

Use caution when prescribing SUFLAVE for patients with a history of seizures and in patients at increased risk of seizure, such as patients taking medications that lower the seizure threshold (e.g., tricyclic antidepressants), patients withdrawing from alcohol or benzodiazepines, or patients with known or suspected hyponatremia [see Drug Interactions (7.1)] .

5.4 Use in Patients with Risk of Renal Injury

Use SUFLAVE with caution in patients with impaired renal function or patients taking concomitant medications that may affect renal function (such as diuretics, angiotensin converting enzyme inhibitors, angiotensin receptor blockers, or non-steroidal anti-inflammatory drugs) [see Drug Interactions (7.1)] . These patients may be at risk for renal injury. Advise these patients of the importance of adequate hydration with SUFLAVE and consider performing baseline and postcolonoscopy laboratory tests (electrolytes, creatinine, and BUN) in these patients [see Use in Specific Populations (8.6)] .

5.5 Colonic Mucosal Ulcerations and Ischemic Colitis

Osmotic laxative products may produce colonic mucosal aphthous ulcerations, and there have been reports of more serious cases of ischemic colitis requiring hospitalization. Concurrent use of stimulant laxatives and SUFLAVE may increase these risks [see Drug Interactions (7.3)] . Consider the potential for mucosal ulcerations resulting from the bowel preparation when interpreting colonoscopy findings in patients with known or suspect inflammatory bowel disease.

5.6 Use in Patients with Significant Gastrointestinal Disease

If gastrointestinal obstruction or perforation is suspected, perform appropriate diagnostic studies to rule out these conditions before administering SUFLAVE [see Contraindications (4)] .

Use with caution in patients with severe active ulcerative colitis.

5.7 Aspiration

Patients with impaired gag reflex or other swallowing abnormalities are at risk for regurgitation or aspiration of SUFLAVE. Observe these patients during administration of SUFLAVE.

Do not combine SUFLAVE with starch-based thickeners [see Dosage and Administration (2.1)] . Polyethylene glycol (PEG), a component of SUFLAVE, when mixed with starch-thickened liquids reduces the viscosity of the starch-thickened liquid. When a PEG-based product used for another indication was mixed in starch-based pre-thickened liquids used in patients with dysphagia, thinning of the liquid occurred and cases of choking and potential aspiration were reported.

5.8 Hypersensitivity Reactions

SUFLAVE contains polyethylene glycol (PEG) and other ingredients that may cause serious hypersensitivity reactions including anaphylaxis, angioedema, rash, urticaria, and pruritus [see Adverse Reactions (6.2)] . Inform patients of the signs and symptoms of anaphylaxis, and instruct them to seek immediate medical care should signs and symptoms occur.

6 ADVERSE REACTIONS

The following serious or otherwise important adverse reactions for bowel preparations are described elsewhere in the labeling:

- Serious Fluid and Electrolyte Abnormalities [see Warnings and Precautions (5.1)]
- Cardiac Arrhythmias [see Warnings and Precautions (5.2)]
- Seizures [see Warnings and Precautions (5.3)]
- Patients with Risk of Renal Injury [see Warnings and Precautions (5.4)]
- Colonic Mucosal Ulceration and Ischemic Colitis [see Warnings and Precautions (5.5)]
- Patients with Significant Gastrointestinal Disease [see Warnings and Precautions (5.6)]
- Aspiration [see Warnings and Precautions (5.7)]
- Hypersensitivity Reactions [see Warnings and Precautions (5.8)]

6.1 Clinical Trials Experience

Because clinical studies are conducted under widely varying conditions, adverse reaction rates observed in the clinical trials of a drug cannot be directly compared to rates in clinical trials of another drug and may not reflect the rates observed in practice.

The safety of SUFLAVE was evaluated in two randomized, parallel group, multicenter, investigator-blinded clinical trials in 929 adult patients undergoing colonoscopy. The active comparators were polyethylene glycol 3350, sodium sulfate, sodium chloride, potassium chloride, ascorbic acid and sodium ascorbate for oral solution in Study 1 and sodium sulfate, potassium sulfate, and magnesium sulfate oral solution in Study 2 [see Clinical Studies (14)] .

Table 1 shows the most common adverse reactions reported in at least 2% of patients in either treatment group in Study 1.

Table 1: Common Adverse Reactionsa by Treatment Group in Adult Patients Undergoing Colonoscopy in Study 1b
 | SUFLAVE (%) N=233 | Polyethylene glycol 3350, sodium sulfate, sodium chloride, potassium chloride, ascorbic acid and sodium ascorbate for oral; solution (%) N=243
Nausea | 13 | 9
Abdominal distension | 6 | 3
Vomiting | 6 | 3
Abdominal painc | 3 | 4
Headache | 3 | 2
aReported in at least 2% of patients in either treatment group.
bStudy 1 was not designed to support comparative claims for SUFLAVE for the adverse reactions reported in this table.
cAbdominal pain is composed of several similar terms.

Table 2 shows the most common adverse reactions reported in at least 2% of patients in either treatment group in Study 2.

Table 2: Common Adverse Reactionsa by Treatment Group in Adult Patients Undergoing Colonoscopy in Study 2b
 | SUFLAVE (%) N=227 | Sodium sulfate, potassium sulfate, and magnesium sulfate oral solution (%) N=226
Nausea | 7 | 6
Vomiting | 4 | 7
Headache | 2 | 2
Abdominal painc | 3 | 1
Abdominal distension | 1 | 1
aReported in at least 2% of patients in any treatment group.
bStudy 2 was not designed to support comparative claims for SUFLAVE for the adverse reactions reported in this table.
cAbdominal pain is composed of several similar items.

Laboratory Changes
Electrolyte Abnormalities
In patients with normal baseline values, the most common electrolyte abnormality following study drug, on the day of colonoscopy, was increased magnesium (Study 1: 11% in SUFLAVE-treated patients and 2% in patients treated with active comparator; Study 2: 12% in SUFLAVE-treated patients and 11% in patients treated with active comparator). These changes were transient and resolved without intervention.

Renal Function Parameters
In patients with normal baseline values, at 48 to 72 hours after bowel preparation, an increase in serum creatinine of > 0.3 mg/dL and/or a decrease in eGFR of > 25% were reported in 2% of SUFLAVE-treated patients and 0 patients treated with active comparator in Study 1 and 1% of SUFLAVE-treated patients and 3% of patients treated with active comparator in Study 2. These changes were transient and resolved.

6.2 Postmarketing Experience

The following adverse reactions have been identified during post-approval use of other polyethylene glycol-based products. Because these reactions are reported voluntarily from a population of uncertain size, it is not always possible to reliably estimate their frequency or establish a causal relationship to drug exposure.

Cardiovascular: arrhythmia, atrial fibrillation, peripheral edema, asystole, acute pulmonary edema [see Warnings and Precautions (5.2)] .

Gastrointestinal: upper gastrointestinal bleeding from a Mallory-Weiss tear; esophageal perforation, usually with gastroesophageal reflux disease

Hypersensitivity reactions: rash, urticaria, pruritus, dermatitis, dyspnea, chest tightness and throat tightness, fever, angioedema, anaphylaxis and anaphylactic shock [see Warnings and Precautions (5.8)] .

Nervous system: tremor, seizure [see Warnings and Precautions (5.3)]

7 DRUG INTERACTIONS

7.1 Drugs That May Increase Risks of Fluid and Electrolyte Abnormalities

Use caution when prescribing SUFLAVE to patients taking medications that increase the risk of fluid and electrolyte disturbances or may increase the risk of adverse events of seizure, arrhythmias, and prolonged QT in the setting of fluid and electrolyte abnormalities [see Warnings and Precautions (5.1, 5.2, 5.3, 5.4)] .

7.2 Potential for Reduced Drug Absorption

SUFLAVE can reduce the absorption of other co-administered drugs [see Dosage and Administration (2.1)] :

- Administer oral medications at least one hour before starting each dose of SUFLAVE.
- Administer tetracycline and fluoroquinolone antibiotics, iron, digoxin, chlorpromazine, and penicillamine at least 2 hours before and not less than 6 hours after administration of each dose of SUFLAVE to avoid chelation with magnesium.

7.3 Stimulant Laxatives

Concurrent use of stimulant laxatives and SUFLAVE may increase the risk of mucosal ulceration or ischemic colitis. Avoid use of stimulant laxatives (e.g., bisacodyl, sodium picosulfate) while taking SUFLAVE [see Warnings and Precautions (5.5)] .

8 USE IN SPECIFIC POPULATIONS

8.1 Pregnancy

Risk Summary
There are no available data on the use of SUFLAVE during pregnancy to evaluate for a drug-associated risk of major birth defects, miscarriage, or adverse maternal or fetal outcomes. Animal reproduction studies have not been conducted with polyethylene glycol 3350, sodium sulfate, potassium chloride, magnesium sulfate, and sodium chloride (SUFLAVE).

The estimated background risk of major birth defects and miscarriage for the indicated population is unknown. All pregnancies have a background risk of birth defect, loss, or other adverse outcomes. In the U.S. general population, the estimated background risk of major birth defects and miscarriage in clinically recognized pregnancies is 2% to 4% and 15% to 20%, respectively.

8.2 Lactation

Risk Summary
There are no available data on the presence of SUFLAVE in human or animal milk, the effects of on the breastfed child, or the effects on milk production.

The developmental and health benefits of breastfeeding should be considered along with the mother’s clinical need for SUFLAVE and any potential adverse effects on the breastfed child from SUFLAVE or from the underlying maternal condition.

8.4 Pediatric Use

The safety and effectiveness of SUFLAVE in pediatric patients have not been established.

8.5 Geriatric Use

Of the 460 patients who received SUFLAVE in clinical trials, 125 (27%) were 65 years of age or older. No differences in effectiveness of SUFLAVE were observed between geriatric patients and younger adult patients. Among geriatric patients, decreases in blood pressure on the day of colonoscopy were reported more frequently with SUFLAVE than with the active comparator in Study 1 (6% in SUFLAVE-treated patients and 1% in patients treated with active comparator) in Study 2 (3% in SUFLAVE-treated patients and 0% treated with active comparator) [see Clinical Studies (14)] .

Geriatric patients are more likely to have decreased hepatic, renal or cardiac function and may be more susceptible to adverse reactions resulting from fluid and electrolyte abnormalities [see Warnings and Precautions (5.1)] . Advise geriatric patients to hydrate adequately before, during, and after the use of SUFLAVE.

8.6 Renal Impairment

Use SUFLAVE with caution in patients with renal impairment or patients taking concomitant medications that may affect renal function. These patients may be at risk for renal injury. Advise these patients of the importance of adequate hydration before, during and after use of SUFLAVE and consider performing baseline and post-colonoscopy laboratory tests (electrolytes, creatinine, and BUN) in these patients [see Warning and Precautions (5.4)] .

10 OVERDOSAGE

Overdosage of more than the recommended dose of SUFLAVE may lead to severe electrolyte disturbances, as well as dehydration and hypovolemia, with signs and symptoms of these disturbances [see Warnings and Precautions (5.1, 5.2, 5.3)] . Monitor for fluid and electrolyte disturbances and treat symptomatically.

11 DESCRIPTION

SUFLAVE (polyethylene glycol 3350, sodium sulfate, potassium chloride, magnesium sulfate, and sodium chloride for oral solution) is an osmotic laxative and is provided in two bottles and two flavor enhancing packets for oral solution.

The active ingredients contained in SUFLAVE are provided in Table 3.

Table 3: Active Ingredients in SUFLAVE
Chemical Name | Chemical Formula | Average Molecular Weight (g/mol) | Chemical Structure
Polyethlyene Glycol 3350, USP |  | 3350
Sodium Sulfate, USP | Na2SO4 | 142.04
Magnesium Sulfate, USP | MgSO4 | 120.37
Potassium Chloride, USP | KCl | 74.55
Sodium Chloride, USP | NaCl | 58.44 | Na^+Cl^-

Each bottle contains 178.7 g polyethylene glycol 3350, 7.3 g sodium sulfate, 1.12 g potassium chloride, 0.9 g magnesium sulfate, and 0.5 g sodium chloride, plus the following excipients: advantame, lemon-lime flavor, and neotame.

Each flavor enhancing packet contains anhydrous citric acid, colloidal silicon dioxide, malic acid, and sucralose.

Each dose of reconstituted oral solution is one liter of slightly hazy to hazy liquid that contains 178.7 g polyethylene glycol 3350, 7.3 g sodium sulfate, 1.12 g potassium chloride, 0.9 g magnesium sulfate, and 0.5 g sodium chloride and the following excipients: advantame, anhydrous citric acid, colloidal silicon dioxide, lemon-lime flavor, malic acid, neotame, and sucralose.

12 CLINICAL PHARMACOLOGY

12.1 Mechanism of Action

The primary mode of action is the osmotic effects of polyethylene glycol 3350, sodium sulfate and magnesium sulfate, which induce a laxative effect. The physiological consequence is increased water retention in the lumen of the colon, resulting in loose stools.

12.3 Pharmacokinetics

After administration of the first dose of SUFLAVE in 18 healthy subjects, the mean ± SD maximum plasma concentration (Cmax) for polyethylene glycol 3350 of 3.4 ± 1.4 mcg/mL was reached at 4 hours, and the mean ± SD serum Cmaxfor sulfate of 27.0 ± 11.4 mcg/mL was reached at 6 hours. Following a second dose of SUFLAVE (approximately 12 hours later), the mean ± SD plasma Cmaxfor polyethylene glycol 3350 of 2.9 ± 0.97 mcg/mL was reached at 4 hours, and the mean ± SD serum Cmaxfor sulfate of 29.2 ± 11.0 mcg/mL was reached at 3 hours. Sulfate concentrations were below the limit of quantitation (19.2 mcg/mL) for all subjects by follow-up Day 3. Polyethylene glycol 3350 concentrations were below the limit of quantitation (LOQ 0.01 mcg/mL) for 16 of 18 subjects by follow-up Day 7.

14 CLINICAL STUDIES

The colon cleansing efficacy of SUFLAVE was evaluated in two randomized, single-blind, active-controlled, multicenter trials (Study 1 and Study 2). These trials included adult patients undergoing colonoscopy for colorectal cancer screening and surveillance, or diagnostic colonoscopy, including patients with abdominal pain, diarrhea, constipation and non-severe inflammatory bowel disease.

In Study 1 (NCT04446299), 471 adult patients were included in the efficacy analysis. Patients ranged in age from 20 to 84 years (median age 58 years) and 54% were female. The racial distribution was 70% White, 27% African-American, 2% Asian, and 1% American Indian or Alaska Native. The population was 8% Hispanic or Latino. Patients were randomized to one of the following two colon preparation regimens: SUFLAVE or polyethylene glycol 3350, sodium sulfate, sodium chloride, potassium chloride, ascorbic acid and sodium ascorbate for oral solution. Both preparations were administered according to a split-dose regimen [see Dosage and Administration (2.2)] . Patients receiving SUFLAVE were limited to a low residue breakfast followed by clear liquids on the day prior to the colonoscopy; patients receiving the comparator bowel prep were allowed to have a normal breakfast and a light lunch, followed by clear liquids and/or yogurt for dinner on the day prior to the colonoscopy.

In Study 2 (NCT04446312), 450 adult patients were included in the efficacy analysis. Patients ranged in age from 18 to 80 years (median age 57 years) and 58% were female. The racial distribution was 85% White, 10% African-American, 3% Asian, and < 1% American Indian or Alaska Native. The population was 21% Hispanic or Latino. Patients were randomized to one of the following two colon preparation regimens: SUFLAVE or sodium sulfate, potassium sulfate, and magnesium sulfate oral solution. Both preparations were administered according to a split-dose regimen [see Dosage and Administration (2.2)] . Patients receiving SUFLAVE were limited to a low residue breakfast followed by clear liquids on the day prior to the colonoscopy; patients receiving the comparator bowel prep were allowed a light breakfast followed by clear liquids on the day prior to the colonoscopy.

The primary efficacy endpoint in each trial was the proportion of patients with successful colon cleansing, as assessed by the blinded colonoscopist utilizing the four-point scale described in Table 4. Success was defined as an overall cleansing assessment of 3 (Good) or 4 (Excellent).

Table 4: Description of Colonoscopy Scoring
Score | Grade | Description
1 | Poor | Large amount of fecal residue, additional bowel preparation required.
2 | Fair | Enough feces even after washing and suctioning to prevent clear visualization of the entire colonic mucosa.
3 | Good | Feces and fluid requiring washing and suctioning, but still achieves clear visualization of the entire colonic mucosa.
4 | Excellent | No more than small bits of feces/fluid which can be suctioned easily; achieves clear visualization of the entire colonic mucosa.

Results for the primary endpoint in Studies 1 and 2 are shown in Table 5. In both trials, SUFLAVE was non-inferior to the active comparator.

Table 5: Proportion of Adult Patients with Overall Cleansing Successain Two Controlled Trials with a Split-Dose Regimen
 | SUFLAVE; % (n/N) | Active Comparator; % (n/N) | SUFLAVE-Active Comparator
 |  |  | Differenceb(%) | 99% Confidence; Intervalb
Study 1 | 93%; (215/232) | 89%c; (212/239) | 3.4% | (-1.7%, 8.5%)e
Study 2 | 94%; (212/226) | 94%d; (211/224) | 0.2% | (-4.0%, 4.3%)e
a success was defined as an overall cleaning assessment of 3 (Good) or 4 (Excellent) by the blinded endoscopist, with scores assigned on withdrawal of colonoscope.
b common risk differences and confidence intervals were based on Mantel-Haenszel method adjusting for study site
c active comparator in Study 1 was polyethylene glycol 3350, sodium sulfate, sodium chloride, potassium chloride, sodium ascorbate and ascorbic acid for oral solution
d active comparator in Study 2 was sodium sulfate, potassium sulfate, and magnesium sulfate oral solution
enon-inferiority was demonstrated

16 HOW SUPPLIED/STORAGE AND HANDLING

SUFLAVE (polyethylene glycol 3350, sodium sulfate, potassium chloride, magnesium sulfate, and sodium chloride for oral solution) is supplied as a white powder for reconstitution and is lemon-lime flavored.

Each carton of SUFLAVE (NDC 52268-550-01) contains:

- Two bottles, each bottle (NDC 52268-551-01), closed with child resistant closure, contains a white powder of 178.7 g polyethylene glycol 3350, 7.3 g sodium sulfate, 1.12 g potassium chloride, 0.9 g magnesium sulfate, and 0.5 g sodium chloride for reconstitution. The bottle contains lemon-lime flavor.
- Two flavor enhancing packets (NDC 52268-552-01).

Storage
Store SUFLAVE at room temperature between 20º to 25°C (68º to 77°F), excursions permitted from 15º to 30°C (59º to 86°F). See USP controlled room temperature.

17 PATIENT COUNSELING INFORMATION

Advise the patient to read the FDA-approved patient labeling (Medication Guide and Instructions for Use).

Instruct patients:

- Administration of two doses of SUFLAVE are required for a complete preparation for colonoscopy.
- Must reconstitute each bottle with water before ingestion.
- Must consume an additional 16 ounces of water after each dose of SUFLAVE.
- To hydrate adequately with clear liquids before, during, and after the use of SUFLAVE to prevent dehydration [see Warnings and Precautions (5.1)] . Examples of clear liquids can be found in the Instructions for Use.
- If nausea, bloating, or abdominal cramping occurs, pause or slow the rate of drinking the solution and additional water until symptoms diminish.
- Do not take other laxatives while taking SUFLAVE.
- Do not drink milk or eat or drink anything colored red or purple.
- Do not drink alcohol.
- Do not take oral medications within one hour of starting each dose of SUFLAVE [see Drug Interactions (7.2)] .
- If taking tetracycline or fluoroquinolone antibiotics, iron, digoxin, chlorpromazine, or penicillamine, take these medications at least 2 hours before and not less than 6 hours after administration of each dose of SUFLAVE [see Drug Interactions (7.2)] .
- Complete all SUFLAVE and required water at least two hours prior to colonoscopy.
- Contact their healthcare provider if they develop significant vomiting or signs of dehydration after taking SUFLAVE or if they experience cardiac arrhythmias or seizures [see Warnings and Precautions (5.1, 5.2, 5.3)] .
- Seek immediate medical care if signs and symptoms of a hypersensitivity reaction occur [see Warnings and Precautions (5.8)] .

Manufactured by:

Braintree Laboratories, Inc.
270 Centre Street
Holbrook, MA 02343

Please see www.sebelapharma.com for patent information.
© Braintree Laboratories, Inc.

MEDICATION GUIDE

SUFLAVE®(Soo-FLAVE)

(polyethylene glycol 3350, sodium sulfate, potassium chloride, magnesium sulfate,
and sodium chloride for oral solution)

Read and understand this Medication Guide and the Instructions for Use at least 2 days beforeyour colonoscopy and again before you start taking SUFLAVE.

What is the most important information I should know about SUFLAVE?

SUFLAVE and other bowel preparations can cause serious side effects, including:

Serious loss of body fluid (dehydration) and changes in blood salts (electrolytes) in your blood.

These changes can cause:

- abnormal heartbeats that can cause death.
- seizures.This can happen even if you have never had a seizure.
- kidney problems.

Your chance of having fluid loss and changes in body salts with SUFLAVE is higher if you:

- have heart problems.
- have kidney problems.
- take water pills (diuretics), high blood pressure medication, or non-steroidal anti-inflammatory drugs (NSAIDs).

Tell your healthcare provider right away if you have any of these symptoms of a loss of too much body fluid (dehydration) while taking SUFLAVE:

- vomiting • urinating less often than normal
- dizziness • headache

See “What are the possible side effects of SUFLAVE?” for more information about side effects.

What is SUFLAVE?

SUFLAVE is a prescription medicine used by adults to clean the colon before a colonoscopy. SUFLAVE cleans your colon by causing you to have diarrhea (loose stools). Cleaning your colon helps your healthcare provider see the inside of your colon more clearly during your colonoscopy.

It is not known if SUFLAVE is safe and effective in children.

Do not take SUFLAVE if your healthcare provider has told you that you have:

- a blockage in your bowel (obstruction) or a problem with food moving too slowly through your intestines (ileus).
- an opening in the wall of your stomach or intestine (bowel perforation).
- a very dilated intestine (toxic colitis or toxic megacolon).
- problems with food and fluid emptying from your stomach (gastric retention).
- an allergy to any ingredient in SUFLAVE. See the end of this Medication Guide for a complete list of the ingredients in SUFLAVE.

Before taking SUFLAVE, tell your healthcare provider about all of your medical conditions, including if you:

- have problems with serious loss of body fluid (dehydration) and changes in blood salts (electrolytes).
- have heart problems.
- have stomach or bowel problems including ulcerative colitis.
- have problems with swallowing, gastric reflux, or if you inhale food or fluid into your lungs when eating or drinking (aspirate).
- have a history of seizures.
- are withdrawing from drinking alcohol or from taking benzodiazepines.
- have a low blood salt (sodium) level.
- have kidney problems.
- are pregnant. It is not known if SUFLAVE will harm your unborn baby. Talk to your healthcare provider if you are pregnant.
- are breastfeeding or plan to breastfeed. It is not known if SUFLAVE passes into your breast milk. You and your healthcare provider should decide if you will take SUFLAVE while breastfeeding.

Tell your healthcare provider about all the medicines you take,including prescription and over-the-counter medicines, vitamins, and herbal supplements.

SUFLAVE may affect how other medicines work. Medicines taken by mouth may not be absorbed properly when taken within 1 hour before the start of each dose of SUFLAVE.

Especially tell your healthcare provider if you take:

- medicines to treat a blood salt (electrolyte) imbalance.
- medicines for blood pressure or heart problems.
- medicines for kidney problems.
- medicines for seizures.
- water pills (diuretics).
- non-steroidal anti-inflammatory drugs (NSAIDs).
- medicines for depression or other mental health problems.
- laxatives. Do nottake other laxatives while taking SUFLAVE.
- starch-based thickeners. For patients who have trouble swallowing, do notmix SUFLAVE with starch-based thickeners.

The following medicines should be taken at least 2 hours before starting each dose of SUFLAVE and not less than 6 hours after taking each dose of SUFLAVE:
• tetracycline • iron • chlorpromazine
• fluoroquinolone antibiotics • digoxin • penicillamine
Ask your healthcare provider or pharmacist for a list of these medicines if you are not sure if you are taking any of the medicines listed above.

Know the medicines you take. Keep a list of them to show your healthcare provider and pharmacist when you get a new medicine.

How should I take SUFLAVE?

See the Instructions for Use for dosing instructions. You must read, understand, and follow these instructions to take SUFLAVE the right way.

- Take SUFLAVE exactly as your healthcare provider tells you to take it.
- Two doses of SUFLAVE are required for a complete colonoscopy preparation. One dose of SUFLAVE is equal to one bottle plus one flavor enhancing packet.
- It is important for you to drink the additional prescribed amount of water listed in the Instructions for Use to prevent fluid loss (dehydration).
- SUFLAVE is taken using the Split-Dosemethod. See the Instructions for Use for more information.
- All people taking SUFLAVE should follow these general instructions starting 1 day before your colonoscopy:
  o you can eat a low-residue breakfast. Low-residue foods include white bread, biscuits, muffins (no wheat), cornflakes, eggs, cream of wheat, grits, yogurt, cottage cheese, coffee, tea, juice without pulp, and fruit (no skin or seeds).
  o after breakfast only drink clear liquids all day and the next day until 2 hours before your colonoscopy. Stop drinking all fluids at least 2 hours before the colonoscopy. Examples of clear liquids include water, fruit juices (without pulp), lemonade, coffee, tea (no cream or non-dairy creamer), chicken broth, and gelatin desserts (no fruit or topping).
  o after taking the first dose of SUFLAVE if you have any nausea, bloating or feeling like your stomach is upset, wait to take your second dose of SUFLAVE until your stomach feels better. Start taking your second dose 5 to 8 hours before the colonoscopy, but no sooner than 4 hours from taking your first dose.
- While taking SUFLAVE, do not:
  o take any other laxatives
  o take oral medicines within 1 hour of starting each dose of SUFLAVE
  o eat solid foods, dairy such as milk, or drink alcohol
  o eat or drink anything colored red or purple

Contact your healthcare provider right awayif after taking SUFLAVE you have severe vomiting, signs of too much fluid loss (dehydration), abnormal heartbeats or seizures.

What are the possible side effects of SUFLAVE?

SUFLAVE can cause serious side effects, including:

- See "What is the most important information I should know about SUFLAVE?"
- Changes in certain blood tests.Your healthcare provider may do blood tests after you take SUFLAVE to check your blood for changes. Tell your healthcare provider if you have any symptoms of too much fluid loss, including:
  o vomiting o nausea o bloating
  o dizziness o stomach (abdominal) o headache
  o urinate less than usual cramping
  o trouble drinking clear liquid
- Heart problems. SUFLAVE may cause abnormal heartbeats.
- Seizures.
- Ulcers of the bowel or bowel problems (ischemic colitis).Tell your healthcare provider right away if you have severe stomach-area (abdominal) pain or rectal bleeding.
- Serious allergic reactions. Get medical help right away if you have any signs and symptoms of a serious allergic reaction while taking SUFLAVE including:
  o difficulty breathing o itching
  o swelling of the face, lips, taongue and throat o raised red patches on your skin (hives)
  o skin rash

The most common side effects of SUFLAVE include:
• nausea • stomach (abdominal) pain
• stomach bloating (abdominal distention) • headache

• vomiting
These are not all the possible side effects of SUFLAVE.

Call your doctor for medical advice about side effects. You may report side effects to FDA at 1-800-FDA-1088.

How should I store SUFLAVE?

- Store SUFLAVE at room temperature between 68°F to 77°F (20°C to 25°C).
- Store mixed (reconstituted) SUFLAVE solution in the refrigerator at 36°F to 46°F (2°C to 8°C). Do not freeze.
- Used mixed (reconstituted) SUFLAVE solution within 24 hours.
- After 24 hours, throw away (discard) any mixed (reconstituted) SUFLAVE solution that is not used.

Keep SUFLAVE and all medicines out of the reach of children.

General information about the safe and effective use of SUFLAVE.

Medicines are sometimes prescribed for purposes other than those listed in a Medication Guide. Do not use SUFLAVE for a condition for which it was not prescribed. Do not give SUFLAVE to other people, even if they are going to have the same procedure you are. It may harm them.

You can ask your pharmacist or healthcare provider for information that is written for health professionals.

What are the ingredients in SUFLAVE?

Active ingredients: polyethylene glycol 3350, sodium sulfate, potassium chloride, magnesium sulfate, and sodium chloride.

Inactive ingredients: advantame, anhydrous citric acid, colloidal silicon dioxide, lemon-lime flavor, malic acid, neotame, and sucralose.

Manufactured by:

Braintree Laboratories, Inc.
270 Centre Street
Holbrook, MA 02343
For more information, go to www.braintreelabs.comor call 1-800-874-6756.

This Medication Guide has been approved by the U.S. Food and Drug Administration. Issued 06/2023

Principal Display Panel - Carton Label

NDC 52268-550-01

Dispense the enclosed Medication Guide to each patient.

SUFLAVE
(polyethylene glycol 3350, sodium sulfate, potassium chloride, magnesium sulfate, and sodium chloride for oral solution)
178.7g/7.3g/1.12 g/0.9g/0.5g

2 Doses of SUFLAVE are required for a complete preparation.

This carton contains:
2 Flavor Enhancing Packets
2 Bottles
1 Patient booklet, which includes:
1. Instructions for Use
2. Full Prescribing Information
3. Medication Guide

© 2023 Braintree Labroatories, Inc. All rights reserved. 6/2023

Rx only

Braintree
A PART OF SEBELA PHARMACEUTICALS®

Principal Display Panel - Bottle Label

NDC 52268-551-01

SUFLAVE(polyethylene glycol 3350, sodium sulfate, potassium chloride, magnesium sulfate, and sodium chloride for oral solution)

178.7g/7.3g/1.12 g/0.9g/0.5g

Dispense the enclosed Medication Guide to each patient.

2 Doses of SUFLAVE are required for a complete preparation.

Rx only

Net Weight 188.73 g

PACKAGE LABEL

Principal Display Panel - Flavor Enhancing Packet

NDC 52268-552-01

SUFLAVE

For use with 1 SUFLAVE Bottle

This packet contains:
citric acid, anhydrous, USP, 0.820 g;
colloidal silicon dioxide, NF, 0.009 g;
malic acid, FCC, 0.718 g;
sucralose, FCC, 0.300 g.

Dispense the enclosed Medication Guide to each patient.

Net Weight 1.847 g